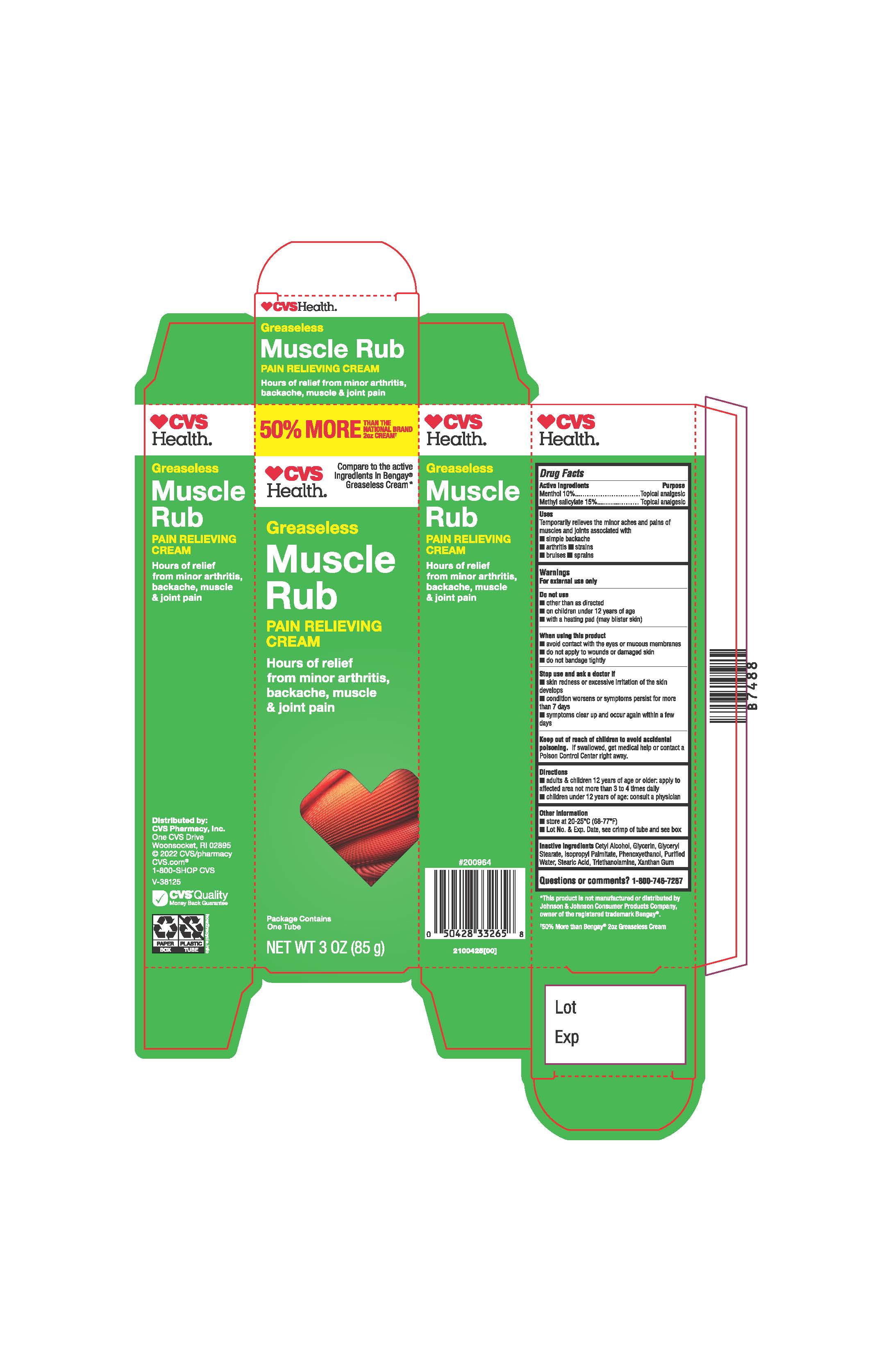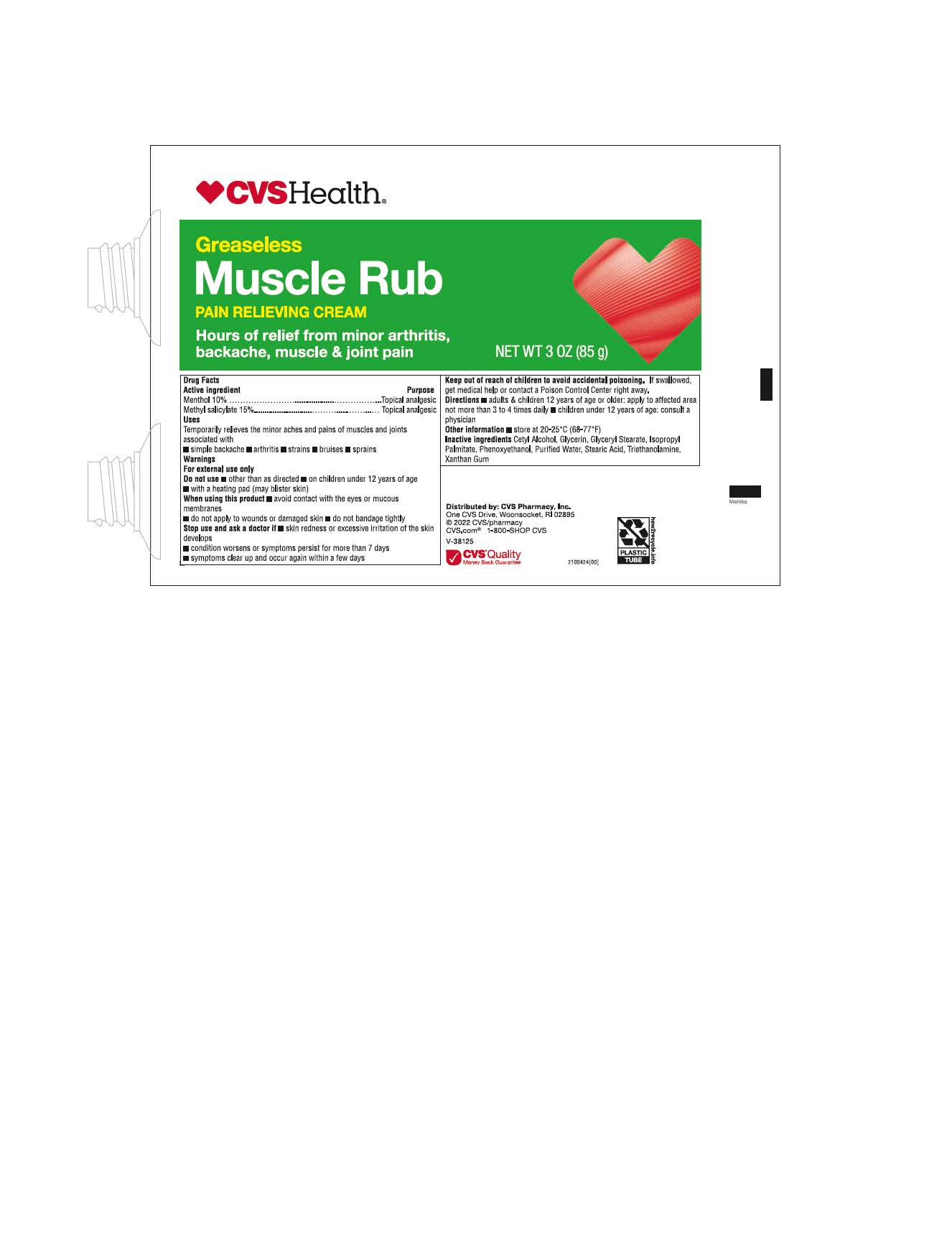 DRUG LABEL: CVS Muscle Rub
NDC: 51316-994 | Form: CREAM
Manufacturer: CVS Health
Category: otc | Type: HUMAN OTC DRUG LABEL
Date: 20241211

ACTIVE INGREDIENTS: METHYL SALICYLATE 150 mg/1 g; MENTHOL 100 mg/1 g
INACTIVE INGREDIENTS: GLYCERYL MONOSTEARATE; STEARIC ACID; PHENOXYETHANOL; TROLAMINE; GLYCERIN; WATER; XANTHAN GUM; CETYL ALCOHOL; ISOPROPYL PALMITATE

CVS Muscle Rub

ACTIVE INGREDIENT

Menthol 10%

Methyl Salicylate 15%

PURPOSE

Topical analgesic

INDICATIONS AND USAGE

Temporarily relieves the minor aches and pains of muscle and joints associated with

Simple backache

arthritis

strains

bruises

sprains

WARNINGS

For External use only

Do not use

other than as directed

on children under 12 years of age

with a heating pad (may blister skin)

When using this product

avoid contact with the eyes or mucous membranes

do not apply to wounds or damaged skin

do not bandage tightly

Stop use and ask a doctor if

skin redness or excessive irritation of the skin develops

condition worsens or symptoms persist for more than 7 days

symptoms clear up and occur again within a few days

Keep out of reach of children to avoid accidental poisoning

If swallowed , get medical help or contact a Poison Control Center right away

DOSAGE AND ADMINISTRATION

adults and children 12 years of age or older: apply to affected area not more than 3 to 4 times daily

children under 12 years of age: consult a physician

OTHER SAFETY INFORMATION

Store at 20 - 25°C (68-77°F)

Lot No. & Exp. Date, see crimp of tube and see box

INACTIVE INGREDIENT

Cetyl Alcohol, Glycerin, Glyceryl Stearate, Isopropyl Palmitate, Phenoxyethanol, Purified Water, Stearic Acid, Triethanolamine, Xanthan Gum

QUESTIONS

1-800-746-7287